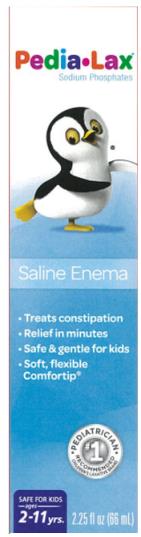 DRUG LABEL: Pedia-Lax
NDC: 0132-0202 | Form: ENEMA
Manufacturer: C.B. Fleet Company, Inc.
Category: otc | Type: HUMAN OTC DRUG LABEL
Date: 20241212

ACTIVE INGREDIENTS: SODIUM PHOSPHATE, DIBASIC, HEPTAHYDRATE 3.5 g/66 mL; sodium phosphate, monobasic 9.5 g/66 mL
INACTIVE INGREDIENTS: EDETATE DISODIUM; WATER; BENZALKONIUM CHLORIDE

Pedia-Lax Enema Saline Laxative 0132-0202

PEDIA-LAX sodium phosphates Saline Enema
C.B. Fleet Company, Inc.

----------

Drug Facts

Active Ingredients

(in each 59-mL delivered dose)

Monobasic Sodium Phosphate 9.5 g................

Dibasic Sodium Phosphate 3.5 g........................

Purpose

Saline laxative

Saline laxative

Use

for relief of occasional constipation.

Warnings

For rectal use only.

Dosage Warning:

Using more than one enema in 24 hours can be harmful.

Do not use without asking a doctor:

- for more than 3 days
- if your child has a kidney disease
- if your child has heart problems
- if your child is dehydrated

Ask a doctor before using this product if the child

- is on a sodium-restricted diet

Ask a doctor before using any laxative if your child has

- abdominal pain, nausea, or vomiting
- a sudden change in bowel habits lasting more than 2 weeks
- already used a laxative for more than 1 week

Stop use and ask a doctor if your child has

- rectal bleeding
- no bowel movement or no liquid comes out of the child’s rectum after 30 minutes
- symptoms of dehydration [feeling thirsty, dizziness, vomiting, urinating less often than normal]

These symptoms may indicate a serious condition.

Keep out of reach of children to prevent accidental ingestion.

If swallowed, get medical help or contact a Poison Control Center right away.

Directions

Single Daily Dosage (per 24 hours)
Do not use more per day unless directed by a doctor. See Warnings.
Do not use if child is taking another sodium phosphates product.

Age | Dose
children 5 to 11 years | 1 bottle per day or as directed by doctor
children 2 to under 5 years | one-half bottle per day (see below)
children under 2 years | DO NOT USE

One-half bottle preparation:
Unscrew cap and remove 2 tablesppons of liquid with a measuring spoon. Replace cap and follow “How to use this enema” directions.

Other information

- each 59-mL delivered dose contains: sodium 2.2g
- additional liquids by mouth are recommended while taking this product
- this product usually produces a bowel movement in 1-5 minutes
- BOTTLE SEALED FOR SAFETY. IF BOTTLE WRAPPER WITH FLEET® EMBLEM IS TORN, DAMAGED, OR MISSING, DO NOT USE
- for complete professional use, warnings and precautions, consult the Reference Safety Information on our website

Inactive Ingredients

benzalkonium chloride, disodium EDTA, purified water

Questions?

1-866-255-6960

www.pedia-lax.com

Fleet® Enemas are LATEX-FREE

PRINCIPAL DISPLAY PANEL

Pedia-Lax
Sodium Phosphates
Saline Enema
2.25 fl oz (66 mL)